DRUG LABEL: Standardized Short Ragweed Pollen
NDC: 49288-0448 | Form: INJECTION, SOLUTION
Manufacturer: Antigen Laboratories, Inc.
Category: prescription | Type: HUMAN PRESCRIPTION DRUG LABEL
Date: 20090821

ACTIVE INGREDIENTS: AMBROSIA ARTEMISIIFOLIA POLLEN 100000 [AU]/1 mL
INACTIVE INGREDIENTS: GLYCERIN 0.525 mL/1 mL; SODIUM CHLORIDE 0.0095 g/1 mL; SODIUM BICARBONATE 0.0024 g/1 mL; WATER

Allergenic Extract

WARNINGS
Standardized Short Ragweed allergenic extract is intended for use by, or under the guidance of, physicians who are experienced in the administration of allergenic extracts for diagnosis and/or immunotherapy and the emergency care of anaphylaxis. Patients being switched from other manufacturers’ extracts to Antigen Laboratories' allergenic extracts should be started as though they were receiving treatment for the first time.(See “WARNINGS” section below.) Severe systemic reactions may occur with all allergenic extracts. In certain individuals, these life-threatening reactions may result in death. Patients should be observed for at least 20 minutes following allergenic extract injections. Treatment and emergency measures, as well as personnel trained in their use, must be available in the event of a life-threatening reaction. Sensitive patients may experience severe anaphylactic reactions resulting in respiratory obstruction, shock, coma and/or death. Patients being switched from one lot of extract to another lot from the same manufacturer should have the dose reduced by 75%.
Report serious adverse events to MedWatch, 5600 Fishers Lane, Rockville, MD 20852-9787, phone 1-800-FDA-1088.
Allergenic extracts should not be injected intravenously. Deep subcutaneous routes have proven to be safe. See the “WARNINGS”, “PRECAUTIONS”, “ADVERSE REACTIONS” and “OVERDOSAGE” sections.
Patients receiving beta-blockers may not be responsive to epinephrine or inhaled bronchodilators. Patients with respiratory obstruction not responding to parenteral or inhaled bronchodilators may require theophylline, oxygen, intubation and life support systems. Parenteral fluid and/or plasma expanders may be utilized for treatment of shock. Adrenocorticosteroids may be administered parenterally or intravenously. Refer to “ADVERSE REACTIONS” section.

DESCRIPTION
Antigen Laboratories’ Standardized Short Ragweed allergenic extracts are sterile and intended for dilution prior to skin testing and/or immunotherapy. The route of administration for immunotherapy is subcutaneous. The routes of administration for diagnostic purposes are intradermal or prick-puncture of the skin.
Standardized Short Ragweed allergenic extract is assigned arbitrary Allergy Units of 100,000 AU/ml based on being equipotent by Enzyme-Linked Immunosorbent Assay (ELISA) to a Center for Biologics Evaluation and Research (CBER) reference.
The following testing is also performed:
1. Microscopic examination to confirm identity and purity of source pollen.
2. Isoelectric focusing (IEF) pattern of source material and final products are compared to respective CBER reference extract.
3. Antigen E (Amb a I) is considered to be the major allergenic protein of short ragweed. The Antigen E content of short ragweed extracts is determined by radial immunodiffusion assay using CBER standards and anti-serum. Standardized Short Ragweed (100,000 AU/ml) extracts contain 200-400 antigen E units per milliliter.
4. Ninhydrin protein analysis.
5. Glycerine analysis.
6. Sterility testing.
7. Safety testing.
Active ingredients: Allergens are described by common and scientific name on container label. Preservative is 50% v/v glycerine. Inactive ingredients are 0.95% sodium chloride, 0.24% sodium bicarbonate and water for injection.

CLINICAL PHARMACOLOGY
The most clinically relevant mechanism of allergenic response begins with cross-linking of plasma membrane receptor-bound IgE molecules by specific antigens causing mast cell mediator release. In vitro, this process is temperature dependent, requires the presence of divalent cations, and activation of a cell membrane-associated serine esterase. Another immunologic mechanism for mast cell degranulation is mediated by complement-derived anaphylatoxins C3a, C4a and C5a. These low molecular weight peptides presumably stimulate degranulation of mast cells by binding to distinct plasma membrane receptor(s) and are active mast cell secretagogues in human skin in vivo. Several naturally occurring and exogenous agents are capable of degranulating and/or stimulating mast cells by nonimmunologic mechanisms.
Stimulation of mast cells leads to the release and generation of pharmacologically active soluble factors that produce immediate hypersensitivity reactions. Some mediators are rapidly liberated from mast cells granules (e.g., histamine), others remain granule-associated after release from the cell (e.g., heparin). Products of arachidonic acid metabolism are rapidly produced and released from mast cells following stimulation. Select patients demonstrate later reactions (i.e., late-phase reactions) at sites of mast cell degranulation. These reactions begin 2 to 8 hours after mediator release and are characterized by granulocyte-rich infiltrates that are followed by accumulations of mononuclear cells. Clinically these late-phase reactions present as inflammatory, infiltrated plaques or nodules.^15
Patients who react to a small quantity of antigen by skin testing, or have a high RAST score, are classified as highly sensitive. Those who react only to large quantities of antigen, or have a low RAST score, are classified as less sensitive. It appears there is at least a 50,000-fold range between the most and least sensitive individuals. Certain patients who do not have elevated quantities of allergen specific IgE, and are RAST negative, do have positive skin tests and have symptoms of allergic rhinitis. These patients are considerably less sensitive than patients with detectable levels of specific IgE antibody.^2
The mode of action of immunotherapy with allergenic extracts is still under investigation. Increasing subcutaneous injection doses of allergenic extract into patients with allergenic disease has shown to result in both humoral and cellular changes. These include production of allergen specific IgG antibodies, suppression of histamine release from target cells, decrease in circulating levels of antigen specific IgE antibody over long periods of time and suppression of peripheral blood T-lymphocyte cell response to antigen.^(5, 9, 10)

INDICATIONS AND USAGE
Allergenic extract is indicated for diagnostic testing and treatment (immunotherapy) of patients whose histories indicate allergic symptoms upon natural exposure to short ragweed pollen. Confirmation is determined by skin testing.

CONTRAINDICATIONS
Do not administer in the presence of diseases characterized by bleeding diathesis. Individuals with autoimmune disease may be at risk of exacerbating symptoms of the underlying disease, possibly due to routine immunization. Recent myocardial infarction patients may not tolerate immunotherapy. Children with nephrotic syndrome probably should not receive injections due to a possibility of immunization causing exacerbation of their nephrotic disease.
Standardized Short Ragweed extract is not intended for the treatment of patients who do not experience allergic symptoms upon natural exposure to the allergen.
Allergenic extracts are not intended for diagnosing patients whose skin does not manifest immediate hypersensitivity reactions (wheal and flare) to the allergenic extract.

WARNINGS
Refer to boxed “WARNINGS”, “PRECAUTIONS”, “ADVERSE REACTIONS” and “OVERDOSAGE” sections.
Extreme caution is necessary when using diagnostic skin tests or injection treatment in highly sensitive patients who have experienced severe symptoms or anaphylaxis by natural exposure or previous skin testing or treatment. IN THESE CASES THE POTENCY FOR SKIN TESTS AND THE ESCALATION OF THE TREATMENT DOSE MUST BE ADJUSTED TO THE PATIENT’S SENSITIVITY AND TOLERANCE.
Benefit versus risk needs to be evaluated in patients with unstable asthma, steroid dependent asthmatics or patients with underlying cardiovascular disease.
Injections should never be given intravenously. A 5/8 inch, 25 gauge needle on a sterile syringe allows deep subcutaneous injection. Withdraw plunger slightly after inserting needle to determine if a blood vessel has been entered.
Proper measurement of dose and caution in making injection will minimize reactions. Adverse reactions to allergenic extracts are usually apparent within 20-30 minutes following injection of immunotherapy.
Extract should be temporarily withheld or dosage reduced in case of any of the following conditions: 1) flu or other infection with fever; 2) exposure to excessive amounts of allergen prior to injection; 3) rhinitis and/or asthma exhibiting severe symptoms; 4) adverse reaction to previous injection until cause of reaction has been evaluated by physician supervising patient’s immunotherapy program.

PRECAUTIONS
General:
Immunotherapy must be given under physician’s supervision. Sterile solutions, vials, syringes, etc. must be used. Observe aseptic technique when making dilutions from stock concentrates, preparing individual treatment doses or during skin testing and administering immunotherapy. The usual precautions in administering allergenic extracts are necessary, refer to boxed WARNINGS and “WARNINGS” section. Sterile syringe and needle must be used for each individual patient to prevent transmission of serum hepatitis, Human Immunodeficiency Virus (HIV) and other infectious agents.
Epinephrine 1:1000 should be available. Refer to “OVERDOSAGE” section for description of treatment for anaphylactic reactions.
Information for Patients:
Patient should remain under observation of a nurse, physician, or personnel trained in emergency measures for at least 20 minutes following immunotherapy injection. Patient must be instructed to report any adverse reactions that occur within 24 hours after injection. Immediate medical attention must be sought for reactions that occur during or after leaving physician’s office.
Pregnancy Category C:
Animal reproduction studies have not been conducted with allergenic extracts. It is not known whether allergenic extracts cause fetal harm during pregnancy or affect reproductive capacity. A systemic reaction to allergenic extracts could cause uterine contractions leading to spontaneous abortion or premature labor. Allergenic extracts should be used during pregnancy only if potential benefit justifies potential risk to fetus.^6
Nursing Mothers:
It is not known whether allergenic extracts are excreted in human milk. Because many drugs are excreted in human milk, caution should be exercised when allergenic extracts are administered to a nursing woman.
Pediatric Use:
Allergenic extracts have been used routinely in children and no special problems of safety or specific hazard have been found. Children can receive the same dose as adults. Discomfort is minimized by dividing the dose in half and administering injection at two different sites.^(13, 14)
Carcinogenesis, Mutagenesis, Impairment of Fertility:
Long term animal studies have not been conducted with Standardized Short Ragweed allergenic extracts to evaluate carcinogenicity, mutagenicity or fertility impairment.
Drug Interactions:
Antihistamines. The H1 antagonists which block the capillary effects of histamine, inhibit the wheal-and-flare reaction. Moreover, H1 antagonists reduce the wheal reaction induced by mast cell secretagogues or allergens in sensitized patients. The most potent H1 antagonist seems to be astemizole, which blocks the wheal and flare induced by histamine for a long period of time, ranging from a few days to 40 days. Although a large interpatient variation exists, hydroxyzine and clemastine seem to be more potent inhibitors than chlorpheniramine, and promethazine. On the other hand, tripelennamine, diphenhydramine, cyproheptadine, and perphenazine induce a variable, but rather low, degree of inhibition. The duration of the inhibitory effect varies from 1 day to up to 10 days, according to the drug and the patient’s sensitivity. Hydroxyzine and clemastine usually exhibit a longer blockade. Sustained-release H1 antagonists may produce a longer inhibitory effect. Long-term treatment with antihistamines may reduce the inhibitory effects of these drugs on skin tests. Long et al. noticed that after 3 weeks of treatment with hydroxyzine, its suppressive effect, as well as that induced by other H1 blockers, was significantly reduced. These data indicate that the 24-hour period without antihistamine sometimes recommended prior to skin testing may not be sufficient for reliable testing. If the histamine control is normal, it suggests that accurate testing can be performed, because the reactions to histamine and allergen were found to be equally suppressed by hydroxyzine.^1,11
Tricylic antidepressents exert a potent and sustained decrease of skin reactions to histamine. This effect may last for a few weeks. Tranquilizers and antiemetic agents of the phenothiazine class have H1 antihistaminic activity and can block skin tests.^1
Corticosteroids. Short-term (less than 1 week) administration of corticosteroids at the therapeutic doses used in asthmatic patients does not modify the cutaneous reactivity to histamine, compound 48/80, or allergen. Long-term corticosteroid therapy modifies the skin texture and makes the interpretation of immediate skin tests more difficult.^1
Theophylline. It appears that theophylline need not be stopped prior to skin testing.^1
Beta-blockers. PATIENTS RECEIVING BETA-BLOCKERS MAY NOT BE RESPONSIVE TO EPINEPHRINE OR INHALED BRONCHODILATORS. The following are commonly prescribed BETA-BLOCKERS: Levatol, Lopressor, Propanolol Intersol, Propanolol HCL, Blocadren, Propanolol, Inderal-LA, Visken, Corgard, Ipran, Tenormin, Timoptic. Ophthalmic beta-blockers: Betaxolol, Levobunolol, Timolol, Timoptic. Chemicals that are beta-blockers and may be components of other drugs: Acebutolol, Atenolol, Esmolol, Metoprolol, Nadolol, Penbutolol, Pindolol, Propanolol, Timolol, Labetalol, Carteolol.
Beta-adrenergic agents. Inhaled beta2 agonists in the usual doses used for the treatment of asthma do not usually inhibit allergen-induced skin tests. However, oral terbutaline and parenteral ephedrine were shown to decrease the allergen-induced wheal. Such an effect seems to be related to the antianaphylactic properties of beta2 agonists and, to a lesser extent, to a direct action on the dermal vasculature. Conversely, beta-blocking agents such as Propanolol can significantly increase skin reactivity.^1
Cromolyn. Cromolyn inhaled or injected prior to skin tests with allergens or degranulating agents does not alter the skin whealing response.^1
Other drugs. Other drugs have been shown to decrease skin test reactivity. Among them, dopamine is the best-documented compound.^1

ADVERSE REACTIONS
Adverse reactions include, but are not necessarily limited to urticaria; itching; edema of extremities; respiratory wheezing or asthma; dyspnea; cyanosis; tachycardia; lacrimation; marked perspiration; flushing of face, neck or upper chest; mild persistent clearing of throat; hacking cough or persistent sneezing.
1) Local Reactions
A mild burning immediately after injection is expected; this usually subsides in 10-20 seconds.
Prolonged pain or pain radiating up arm is usually the result of intramuscular injection, making this injection route undesirable. Subcutaneous injection is the recommended route.
Small amounts of erythema and swelling at the site of injection are common. Reactions should not be considered significant unless they persist for at least 24 hours or exceed 50 mm in diameter.
Larger local reactions are not only uncomfortable, but indicate the possibility of a severe systemic reaction if dosage is increased. In such cases dosage should be reduced to the last level not causing reaction and maintained for two or three treatments before cautiously increasing.
Large, persistent local reactions or minor exacerbations of the patient’s allergic symptoms may be treated by local cold applications and/or use of oral antihistamines.
2) Systemic Reactions
Systemic reactions range from mild exaggeration of patient’s allergic symptoms to anaphylactic reactions.^12 Very sensitive patients may show a rapid response. It cannot be overemphasized that, under certain unpredictable combinations of circumstances, anaphylactic shock is always a possibility. Fatalities are rare but can occur.^16 Other possible adverse reactions include unusual swelling and/or tenderness at injection site, rhinorrhea, sneezing, coughing, wheezing, shortness of breath, nausea, dizziness, fainting, pallor, bradycardia, hypotension, angioedema, conjunctivitis, rhinitis, and urticaria.^8,9
Careful attention to dosage and administration limits such reactions. Allergenic extracts are highly potent to sensitive individuals and OVERDOSE could result in anaphylactic symptoms. Therefore, it is imperative that physicians administering allergenic extracts understand and prepare for treatment of severe reactions. Refer to “OVERDOSAGE” section.

OVERDOSAGE
Refer to “WARNINGS”, “PRECAUTIONS”, and “ADVERSE REACTIONS” sections for signs and symptoms of overdose.
If a systemic or anaphylactic reaction does occur, apply tourniquet above the site of allergenic extract injection and inject intramuscularly or subcutaneously 0.3 to 0.5 ml of 1:1000 Epinephrine-hydrochloride into the opposite arm or gluteal area. Loosen tourniquet briefly at 5 minute intervals to prevent circulatory impairment. Repeat dose in 5-10 minutes if necessary.
The epinephrine HCL 1:1000 dose for infants to 2 years is 0.05 to 0.1 ml; for children 2 to 6 years it is 0.15 ml; for children 6 to 12 years it is 0.2 ml.
Symptoms of progressive anaphylaxis include airway obstruction and/or vascular collapse. After administration of epinephrine, profound shock and vasomotor collapse should be treated with intravenous fluids and possibly vasoactive drugs. Monitor airways for obstruction. Oxygen should be given by mask if indicated.
Antihistamines, H2 antagonist, bronchodilators, steroids and theophylline may be used as indicated after giving adequate epinephrine and circulatory support.^12
Patients who have been taking a beta-blocker may be unresponsive to epinephrine or beta-adrenergic drugs (Alupent). These drugs should be administered even though a beta-blocker may have been taken. The following treatment will be effective whether or not patient is taking a beta-blocker: Aminophylline IV, slow push or drip, Atrovent (Ipratropium bromide) Inhaler, 3 inhalations repeated, Atropine, 0.4 mg/ml, 0.75 to 1.5 ml IM or IV, Solu-Cortef, 100-200 mg IM or IV, Solu-Medrol, 125 mg IM or IV, Glucagon, 0.5-1 mg IM or IV, Benadryl, 50 mg IM or IV, Cimetidine, 300 mg IM or IV, Oxygen via ambu bag.

DOSAGE AND ADMINISTRATION
Refer to “STORAGE” section for proper storage condition for allergenic extract.
Parenteral drug products should be inspected visually for particulate matter and discoloration prior to administration, whenever solution and container permit. Some allergenic extracts naturally precipitate.
Physicians undertaking immunotherapy should be concerned with patient’s degree of sensitivity. The initial dilution of allergenic extract, starting dose, and progression of dosage must be carefully determined on the basis of the patient’s history and results of skin tests. (See “INDICATIONS AND USAGE” section.) Strongly positive skin tests may be risk factors for systemic reactions. Less aggressive immunotherapy schedules may be indicated for such patients.
PRICK-PUNCTURE TESTING: To identify short ragweed sensitive individuals and as a safety precaution, it is recommended that a prick or puncture test be performed prior to initiating very dilute intradermal testing. Prick (puncture) testing is performed by placing a drop of extract on skin and puncturing skin through the drop with a small needle such as a bifurcated vaccinating needle. The most satisfactory sites on the back for skin testing are from posterior axillary fold to 2.5 cm from the spinal column, and from the top of the scapula to the lower rib margins. The best areas on the arms are the volar surfaces from the axilla to 2.5 or 5 cm above the wrist, skipping the anticubital space. A positive reaction is approximately 10-15 mm erythema with 2.5 mm wheal.
Smaller, less conclusive reactions may be considered positive in conjunction with a definitive history of symptoms on exposure to allergen. Less sensitive individuals can be tested intradermally with appropriately diluted extract. (See Intradermal Testing.)
A positive control using histamine phosphate identifies patients whose skin may not react due to medications, metabolic or other reasons. A negative diluent control would exclude false-positive reactions due to ingredients in diluent or patients who have dermatographism.

SERIAL DILUTIONS
APPROXIMATE AU/ml RESULTING FROM 1:5 DILUTION
OF ALLERGENIC EXTRACT CONCENTRATE

DILUTION # | DILUTION EXPONENT | 100,000 AU/ml
No. 1 | 5^-1 | 20,000
No. 2 | 5^-2 | 4,000
No. 3 | 5^-3 | 800
No. 4 | 5^-4 | 160
No. 5 | 5^-5 | 32
No. 6 | 5^-6 | 6.4
No. 7 | 5^-7 | 1.28
No. 8 | 5^-8 | 0.256
No. 9 | 5^-9 | 0.0512
No. 10 | 5^-10 | 0.01024
No. 11 | 5^-11 | 0.002048

SERIAL DILUTIONS
APPROXIMATE AU/ml RESULTING FROM 1:10 DILUTION
OF ALLERGENIC EXTRACT CONCENTRATE

DILUTION # | DILUTION EXPONENT | 100,000 AU/ml
No. 1 | 10^-1 | 10,000
No. 2 | 10^-2 | 1,000
No. 3 | 10^-3 | 100
No. 4 | 10^-4 | 10
No. 5 | 10^-5 | 1
No. 6 | 10^-6 | 0.1
No. 7 | 10^-7 | 0.01
No. 8 | 10^-8 | 0.001
No. 9 | 10^-9 | 0.0001
No. 10 | 10^-10 | 0.00001

INTRADERMAL TESTING: Upper or lower arm is the usual location for skin testing. A sterile, disposable syringe and needle is used for each extract tested. Intracutaneous test dilutions should be made with aqueous diluent. Three-fold, five-fold or ten-fold dilutions may be prepared from stock concentrates. (1) Start testing with the most dilute allergenic extract concentration. (2) A volume of 0.01-0.02 ml should be injected slowly into the superficial skin layers making a small bleb (superficial wheal). (3) An initial skin test with 0.001 AU/ml (10^-8 or 5^-11 dilution) is considered safe for patients with suspected short ragweed sensitivity. Reactions to skin testing are graded 0 to 4+ according to size of wheal and erythema produced (refer to chart below). The reactions should be read after fifteen minutes.

GRADE | mm ERYTHEMA | mm WHEAL
0 | less than 5 | less than 5
+ | 5-10 | 5-10
1+ | 11-20 | 5-10
2+ | 21-30 | 5-10
3+ | 31-40 | 10-15 or with pseudopods
4+ | greater than 40 | greater than 15 or with many pseudopods

If after twenty minutes no skin reaction is observed, continue testing using increments of the concentration until a reaction of 5-10 mm wheal and 10-30 mm erythema is obtained, or a concentration of 5^-2 or 10^-1 has been tested. A positive control of histamine phosphate and a negative control of 50% v/v glycerine diluted with diluent to 5^-2 (1:25) or 10^-1 (1:10) dilution, should be included in interpretation of intradermal testing.^1
INTRADERMAL TESTING--SKIN ENDPOINT TITRATION: Patient’s degree of sensitivity and the initial dose of allergen to be used in immunotherapy can be quantitated using five-fold dilutions of allergenic extract for intracutaneous testing. A concentration of 0.001 AU/ml (5^-11 dilution) is a safe initial dilution. A sequence of 5-fold dilutions of an allergen are injected intracutaneously (0.01-0.02 ml) to form 4 mm diameter superficial wheals. After 15 minutes the endpoint is determined by noting the dilution that first produces a wheal and erythema 2 mm larger than dilutions that produce a 5 mm or negative wheal. The endpoint dilution is used as a starting dose concentration for immunotherapy.
Normally, immunotherapy can be started with 0.15 ml of the dilution of allergenic extract causing the endpoint reaction. In any allergenic patient, a safe starting dose can be determined by finding the first dose by intradermal skin testing producing a 1+ reaction or the dilution producing the skin endpoint.
Increasing doses of 5-20% increments can be administered providing initial or preceding dose is tolerated without significant local reactions. The rate of increase in dosage in the early stages of treatment with highly diluted extracts is usually more rapid than the rate of increase possible with more concentrated extracts. This schedule is intended only as a guide and must be modified to the reactivity of the individual patient. Physicians must proceed cautiously in the treatment of highly sensitive patients who develop large local or systemic reactions.
Some patients may tolerate larger doses of the allergenic extract depending on patient response.^3
Because diluted extract tends to lose activity on storage, the first dose from a more concentrated vial should be the same or less than the previous dose.^4,7
Dosages progressively increase according to the tolerance of the patient at intervals of one to seven days until, (1) the maintenance dose is reached (the “optimal” tolerated dose for each individual); (2) the patient achieves relief of symptoms; (3) induration at the site of injection is no larger than 50 mm in 36 to 48 hours. Maintenance dose may be continued at regular intervals perennially. It may be necessary to adjust the progression of dosage downward to avoid local and systemic reactions during ragweed pollen season.
The usual duration of treatment has not been established. A period of two or three years on immunotherapy constitutes an average minimum course of treatment.
Clinical studies indicate the “optimal” immunotherapy dose of 2000 AU/ml (range of 1000-4000 AU/ml) consistently provides clinical relief for short ragweed sensitive patients. Physician should be forewarned that peak dose in this range is more commonly associated with severe systemic reactions than doses below 1000 AU/ml. Dose may need adjusting downward for extremely sensitive patients or during periods of increased pollen exposure. Patients unable to tolerate target dose should be treated with lower immunizing dose.^1,17

HOW SUPPLIED
Standardized Short Ragweed allergenic extract concentration is expressed in AU/ml. Standardized Short Ragweed (100,000 AU/ml) is supplied in 10, 30 and 50 ml containers. Extracts in 5 ml dropper bottles are available for prick-puncture testing. To insure maximum potency for the entire dating period, all stock concentrates contain 50% v/v glycerine.

STORAGE
Store all stock concentrates and dilutions at 2-8 degrees C. Keep at this temperature during office use. The expiration date of allergenic extracts is listed on the container label. Dilutions of allergenic extracts containing less than 50% v/v glycerine are less stable than those containing at least 50% v/v glycerine. If loss of potency is suspected, potency can be checked using side by side skin testing with freshly prepared dilutions of equal concentration on individuals with known sensitivity to the allergen.

REFERENCES
1. Bousquet, Jean: “In vivo methods for study of allergy: Skin tests” Third Edition, Allergy Principles and Practice, C.V. Mosby Co., Vol. I, Chap. 19, pp 419-436, 1988.
2. Matthews, K., et al: Rhinitis, Asthma and the Other Allergic Diseases. NIAID Task Force Report, U.S. Dept. HEW, NIH Publication No. 79-387, Chapter 4, pp. 213-217, May 1979.
3. Ishizaka, K.: Control of IgE Synthesis, Third Edition, Allergy Principles and Practices, C.V. Mosby Co., Vol. I, Chap. 4, p. 52, 1988.
4. Nelson, H.S.: “The Effect of Preservatives and Dilution on the Deterioration of Russian Thistle (Salsola pestifer), a pollen extract.” The Journal of Allergy and Clinical Immunology, Vol. 63, No. 6, pp. 417-425, June 1979.
5. Rocklin, R.E., Sheffer, A.L., Grainader, D.K. and Melmon, K.: “Generation of antigen-specific suppressor cells during allergy desensitization”, New England Journal of Medicine, Vol. 302, pp. 1213-1219, May 29, 1980.
6. Seebohm, P.M., et al: Panel on Review of Allergenic Extracts, Final Report, Food and Drug Administration, pp. 9-48, March 13, 1981.
7. Stevens, E.: Cutaneous Tests, Regulatory Control and Standardization of Allergenic Extracts, First International Paul Ehrlich Seminar, Frankfurt, Germany, pp. 133-138, May 20-22, 1979.
8. Van Metre, T., Adkinson, N., Amodio, F., Lichtenstein, L., Mardinay, M., Norman, P., Rosenberg, G., Sobotka, A., Valentine, M.: “A Comparative Study of the Effectiveness of the Rinkel Method and the Current Standard Method of Immunology for Ragweed Pollen Hay Fever,” The Journal of Clinical Allergy and Immunology, Vol. 66, No. 6, p. 511, December 1980.
9. Wasserman, S.: The Mast Cell and the Inflammatory Response. The Mast Cell--its role in health and disease. Proceedings of an International Symposium, Davos, Switzerland, Pitman Medical Publishing Co., pp. 9-20, 1979.
10. Perelmutter, L.: IgE Regulation During Immunotherapy of Allergic Diseases. Annals of Allergy, Vol. 57, August 1986.
11. Long, W.F., Taylor, R.J., Wagner, C.J., et al: Skin test suppression by antihistamines and the development of subsensitivity, J. Allergy Clin. Immunol., pp. 76-113, 1985.
12. Wasserman, S., Marquart, D.: Anaphylaxis, Third Edition, Allergy Principles and Practice, C.V. Mosby Co., Vol. 1, Chap. 58, pg. 1365-1376, 1988.
13. Bullock, J., Frick, O.: Mite Sensitivity in House Dust Allergic Children, Am. J. Dis. Child., pp. 123-222, 1972.
14. Willoughby, J.W.: Inhalant Allergy Immunotherapy with Standardized and Nonstandardized Allergenic Extracts, American Academy of Otolaryngology-Head and Neck Surgery: Instructional Courses, C.V. Mosby Co., Vol. 1, Chapter 15, September 1988.
15. Holgate, S.T., Robinson, C., Church, Mike: Mediators of Immediate Hypersensitivity, Third Edition, Allergy Principles and Practice, C.V. Mosby Co., Vol. I and II, pp 135-163, 1988.
16. Reid, Michael J., Lockey, Richard F., Turkeltaub, Paul C., M.D., Platts-Mills, Thomas:”Survey of Fatalities from Skin Testing and Immunotherapy 1985-1989”, Journal of Allergy and Clinical Immunology, Vol. 92, No. 1, pp. 6-15, 1993.
17. Turkeltaub, Paul C., M.D.:”Standardized Extracts in Practice”, Immunotherapy, A Practical Guide to Current Procedures, Sponsored by American Academy of Allergy and Immunology, 1994.